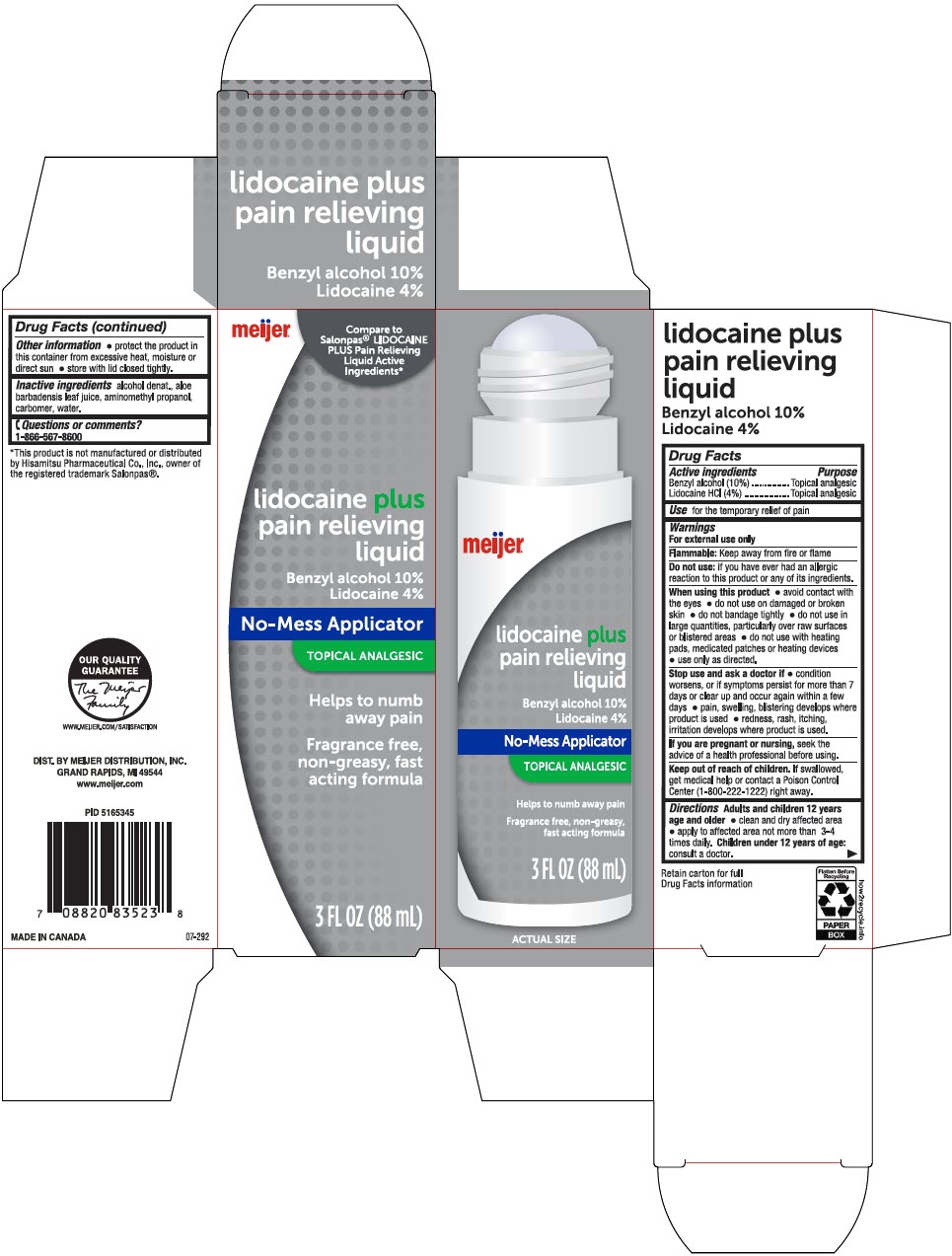 DRUG LABEL: Meijer Pain Lidocaine Plus Relieving
NDC: 79481-0084 | Form: LIQUID
Manufacturer: Meijer Distribution, Inc
Category: otc | Type: HUMAN OTC DRUG LABEL
Date: 20241115

ACTIVE INGREDIENTS: BENZYL ALCOHOL 100 mg/1 mL; LIDOCAINE HYDROCHLORIDE 40 mg/1 mL
INACTIVE INGREDIENTS: ALCOHOL; ALOE VERA LEAF; AMINOMETHYLPROPANOL; CARBOMER HOMOPOLYMER, UNSPECIFIED TYPE; WATER

Meijer Pain Lidocaine Plus Relieving Liquid
Topical Analgesic

Drug Facts

ACTIVE INGREDIENT

Active ingredients | Purpose
Benzyl Alcohol (10%) | Topical analgesic
Lidocaine (HCl 4%) | Topical analgesic

Use

for the temporary relief of pain

Warnings

For external use only

Flammable

Keep away from fire or flame

Do not use

If you ever had an allergic reaction to this product or any of its ingredients.

When using this product

- avoid contact with the eyes
- do not use on damaged or broken skin
- do not bandage tightly
- do not use in large quantities, particularly over raw surfaces or blistered areas
- do not use with heating pads, medicated patches or heating devices
- use only as directed.

Stop use and ask a doctor if

- condition worsens, or if symptoms persist for more than 7 days or clear up and occur again within a few days
- pain, swelling, blistering develops where product is used
- redness, rash, itching, irritation develops where product is used.

PREGNANCY OR BREAST FEEDING

If you are pregnant or nursing, seek the advice of a health professional before using.

Keep out of reach of children. If swallowed, get medical help or contact a Poison Control Center (1-800-222-1222) right away.

Directions

Adults and children 12 years age and older

- clean and dry affected area
- apply to affected area not more than 3 to 4 times daily. Children under 12 years of age: consult a doctor.

Other information

- protect the product in the container from excessive heat, moisture or direct sun
- store with lid closed tightly.

Inactive ingredients

alcohol denat., aloe barbadensis leaf juice, aminomethyl propanol, carbomer, water.

Questions or comments?

1-866-567-8600

DIST. BY MEIJER DISTRIBUTION, INC.
GRAND RAPIDS, MI 49544

PRINCIPAL DISPLAY PANEL - 88 mL Cylinder Carton

meijer®

Compare to
Salonpas® LIDOCAINE
PLUS Pain Relieving
Liquid Active
Ingredients*

lidocaine plus
pain relieving
liquid

Benzyl alcogol 10%
Lidocaine 4%

No-Mess Applicator

TOPICAL ANALGESIC

Helps to numb
away pain

Fragrance free,
non-greasy, fast
acting formula

3 FL OZ (88 mL)